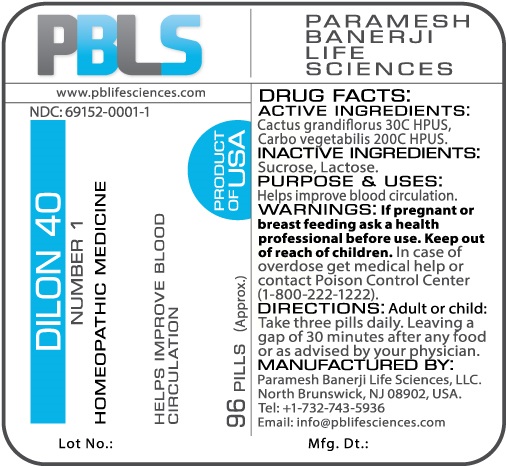 DRUG LABEL: Dilon 40 (Number 1)
NDC: 69152-0001 | Form: PELLET
Manufacturer: Paramesh Banerji Life Sciences LLC
Category: homeopathic | Type: HUMAN OTC DRUG LABEL
Date: 20170215

ACTIVE INGREDIENTS: ACTIVATED CHARCOAL 200 [hp_C]/1 1; SELENICEREUS GRANDIFLORUS STEM 30 [hp_C]/1 1
INACTIVE INGREDIENTS: SUCROSE; LACTOSE

DRUG FACTS: Active Ingredients

Cactus grandiflorus 30C HPUS, Carbo vegetabilis 200C HPUS

Inactive Ingredients

Sucrose, Lactose

Purpose

Helps improve blood circulation

Uses

Helps improve blood circulation

Warnings

If pregnant or breast feeding ask a health professional before use.

Keep out of reach of children. In case of overdose, get medical help or contact a Poison Control Center (1-800-222-1222) right away.

Direction

Adult or child: Take three pills daily. Leaving a gap of 30 minutes after any food or as advised by your physician.

Manufactured by

Paramesh Banerji Life Sciences, LLC.

North Brunswick, NJ 08902, USA.

Tel: +1-732-743-5936

Email: info@pblifesciences.com

Principal Display Panel

NDC: 69152-0001-1

Dilon 40

Number 1

Homeopathic Medicine

Helps improve blood circulation

96 Pills (Approx.)

Product of USA